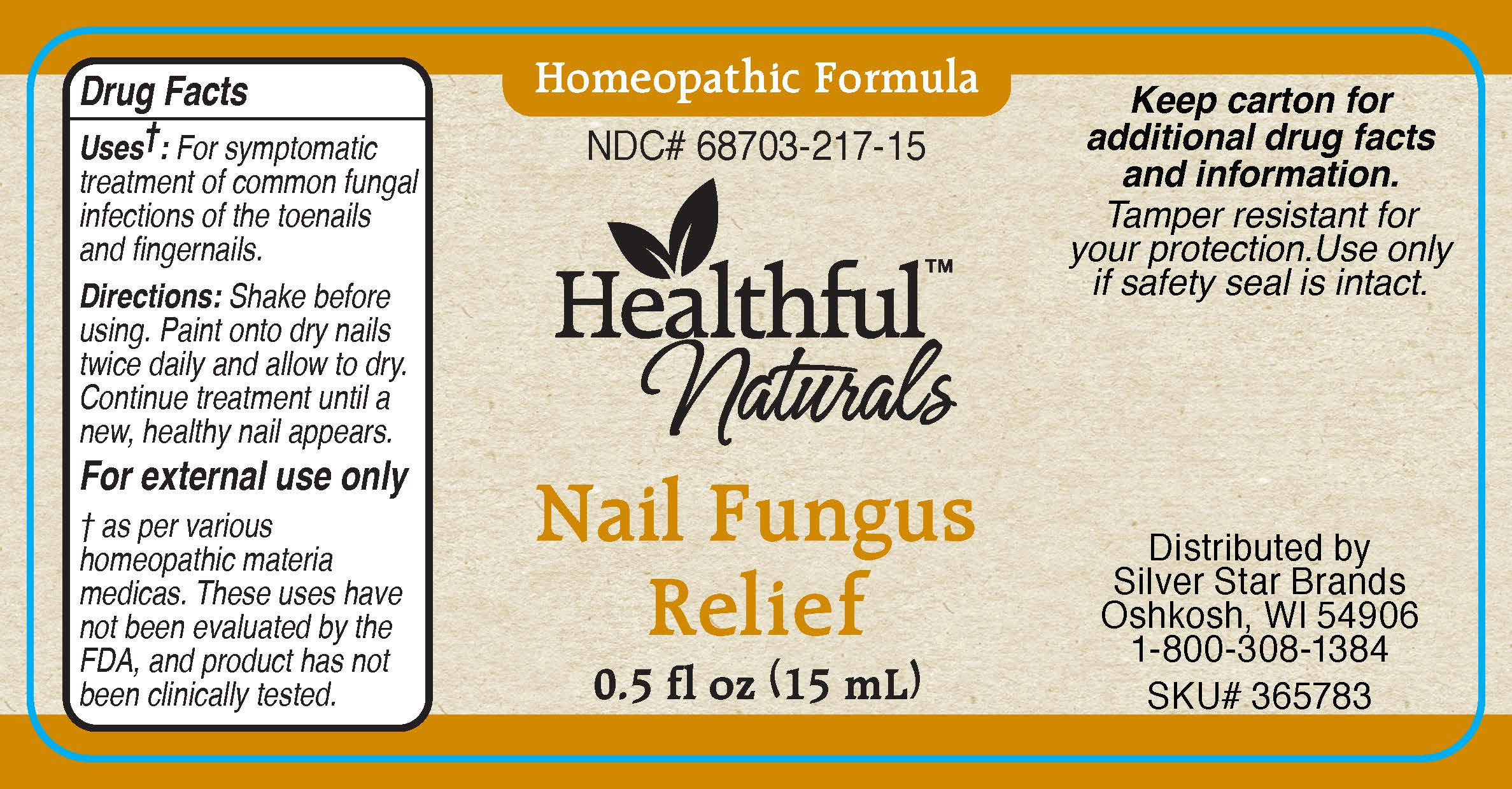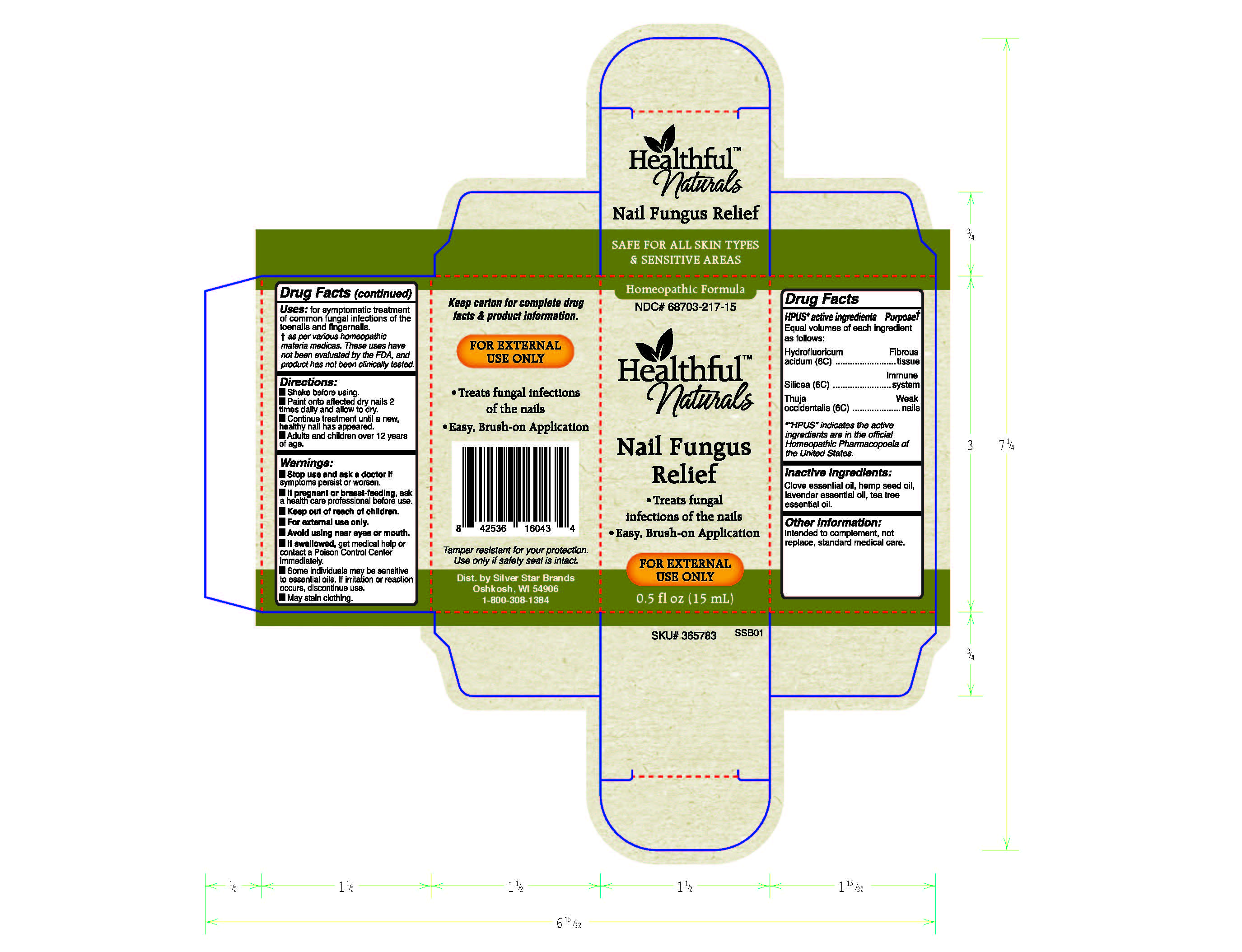 DRUG LABEL: Gout Calm
NDC: 68703-218 | Form: SPRAY
Manufacturer: Silver Star Brands
Category: homeopathic | Type: HUMAN OTC DRUG LABEL
Date: 20230304

ACTIVE INGREDIENTS: ANTIMONY TRISULFIDE 6 [hp_C]/59 mL; BERBERIS VULGARIS FRUIT 30 [hp_C]/59 mL; LITHIUM CARBONATE 6 [hp_C]/59 mL
INACTIVE INGREDIENTS: BLACK PEPPER OIL; GRAPE SEED OIL; BASIL OIL; CELERY SEED OIL

Healthful™ Naturals GoutCalm - 59 ml

HPUS* Active ingredients - Equal volumes of each ingredient as follows: Antimonium crudum (6C), Berberis vulgaris (30C), Lithium carbonicum (6C).

*"HPUS" indicates the active ingredients are in the official Homeopathic Pharmacopoeia of the United States.

Uses+:

Uses+: For symptomatic treatment of gout joint pain and inflammation.

+ As per various homeopathic materia medicas. These uses have not been evaluated by the FDA, and product has not been clinically tested.

Warnings

Warnings: If symptoms persist or worsen, discontinue use immediately and consult a healthcare professional.

If pregnant or breast-feeding, ask a health care professional before use.

Keep out of reach of children.

For external use only.

Avoid using near eyes or mouth.
If swallowed, get medical help or contact a Poison Control Center immediately.

Some individuals may be sensitive to essential oils. If irritation or reaction occurs, discontinue use.

Directions

Directions: Shake well before using.

Spray onto entire affected area and massage into skin every 2 hours until pain begins to subside.

Adults and children over 12 years of age.

Other information:

Intended to complement, not replace, standard medical care.

Tamper resistant for your protection. Use only if safety seal is intact.

Inactive ingredients

Inactive ingredients: Basil essential oil, black pepper essential oil, celery essential oil, grapeseed oil.

Keep out of reach of children.

PREGNANCY OR BREAST FEEDING

If pregnant or breast-feeding, ask a health care professional before use.

HPUS* Active ingredients Purpose+

Equal volumes of each ingredient as follows:

Antimonium crudum (6C)..................................Stiffness, swelling

Berberis vulgaris (30C).....................................Burning pain

Lithium carbonicum (6C)..................................Joint pain